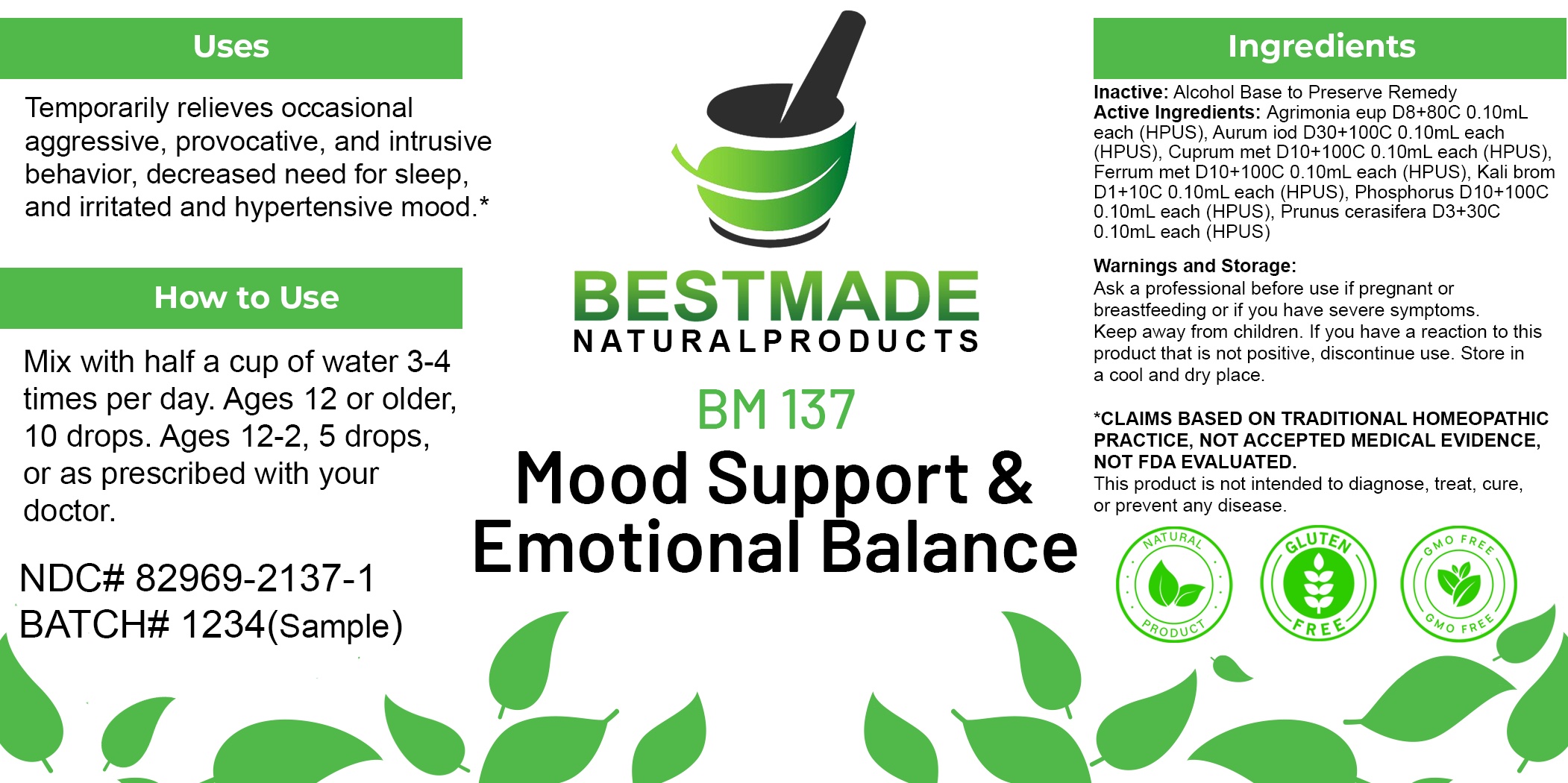 DRUG LABEL: Bestmade Natural Products BM137
NDC: 82969-2137 | Form: LIQUID
Manufacturer: Bestmade Natural Products
Category: homeopathic | Type: HUMAN OTC DRUG LABEL
Date: 20250213

ACTIVE INGREDIENTS: GOLD MONOIODIDE 30 [hp_C]/30 [hp_C]; PRUNUS CERASIFERA FLOWER 30 [hp_C]/30 [hp_C]; COPPER 30 [hp_C]/30 [hp_C]; POTASSIUM BROMIDE 30 [hp_C]/30 [hp_C]; IRON 30 [hp_C]/30 [hp_C]; PHOSPHORUS 30 [hp_C]/30 [hp_C]; AGRIMONIA EUPATORIA WHOLE 30 [hp_C]/30 [hp_C]
INACTIVE INGREDIENTS: ALCOHOL 30 [hp_C]/30 [hp_C]

BM137

DOSAGE AND ADMINISTRATION

How to Use

Mix with half a cup of water 3-4 times per day. Ages 12 or older, 10 drops. Ages 12-2, 5 drops. Ages 2 and under, consult your Doctor.

Inactive:

Alcohol Base to Preserve Product

ACTIVE INGREDIENTS

Agrimonia eup D8+80C 0.10mL each (HPUS), Aurum iod D30+100C 0.10mL each (HPUS), Cuprum met D10+100C 0.10mL each (HPUS), Ferrum met D10+100C 0.10mL each (HPUS), Kali brom D1+10C 0.10mL each (HPUS), Phosphorus D10+100C 0.10mL each (HPUS), Prunus cerasifera D3+30C 0.10mL each (HPUS)

Uses
Temporarily relieves occasional aggressive, provocative, and intrusive behavior, decreased need for sleep, and irritated and hypertensive mood.*

Uses
Temporarily relieves occasional aggressive, provocative, and intrusive behavior, decreased need for sleep, and irritated and hypertensive mood.*

KEEP OUT OF REACH OF CHILDREN

Warnings and Storage:

Ask a professional before use if pregnant or breastfeeding or if you have severe symptoms.

Keep away from children. If you have a reaction to this product that is not positive, discontinue use. Store in a cool and dry place

*CLAIMS BASED ON TRADITIONAL HOMEOPATHIC PRACTICE, NOT ACCEPTED MEDICAL EVIDENCE NOT FDA EVALUATED.
This product is not intended to diagnose, treat, cure, or prevent any disease.

Warnings and Storage:

Ask a professional before use if pregnant or breastfeeding or if you have severe symptoms.

Keep away from children. If you have a reaction to this product that is not positive, discontinue use. Store in a cool and dry place

*CLAIMS BASED ON TRADITIONAL HOMEOPATHIC PRACTICE, NOT ACCEPTED MEDICAL EVIDENCE NOT FDA EVALUATED.
This product is not intended to diagnose, treat, cure, or prevent any disease.

Entire package label